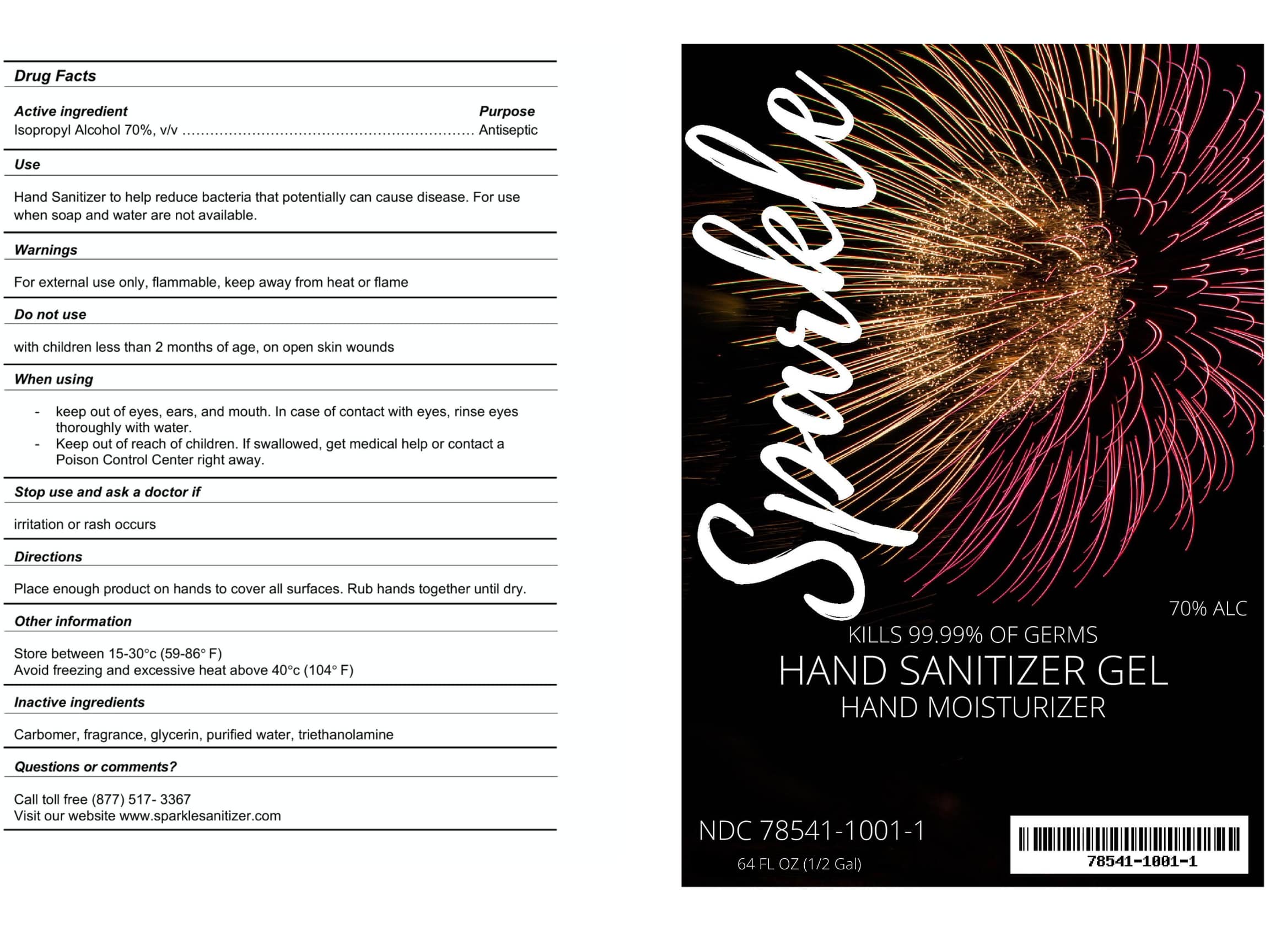 DRUG LABEL: sparkle
NDC: 78541-1001 | Form: GEL
Manufacturer: NBA General Corporation INC
Category: otc | Type: HUMAN OTC DRUG LABEL
Date: 20200918

ACTIVE INGREDIENTS: ISOPROPYL ALCOHOL 70 mL/100 mL
INACTIVE INGREDIENTS: CARBOMER 940 2.5 mL/100 mL; TROLAMINE 0.95 mL/100 mL; GLYCERIN 1.45 mL/100 mL; WATER 24.6 mL/100 mL; FRAGRANCE LAVENDER & CHIA F-153480 0.5 mL/100 mL

Active Ingredient(s)

Isopropyl Alcohol 65% v/v. Purpose: Antiseptic

Use

Hand Sanitizer to help reduce bacteria that potentially can cause disease. For use when soap and water are not available.

Warnings

For external use only. Flammable. Keep away from heat or flame

Do not use

- in children less than 2 months of age
- on open skin wounds

WHEN USING

When using keep out of eyes, ears, and mouth. In case of contact with eyes, rinse eyes thoroughly with water.
Keep out of reach of children. If swallowed, get medical help or contact a Poison Control Center right away.

Stop use and ask a doctor if irritation or rash occurs.

Directions

- Place enough product on hands to cover all surfaces. Rub hands together until dry.

Other information

- Store between 15-30C (59-86F)
- Avoid freezing and excessive heat above 40C (104F)

Inactive ingredients

glycerin, purified water, carbomer, triethanolamine, fragrance

Keep out of reach of children. If swallowed, get medical help or contact a Poison Control Center right away.

PURPOSE

Antiseptic, Hand Sanitizer

Package Label - Principal Display Panel

64 fl oz, 1/2 gal NDC: 78541-1001-1